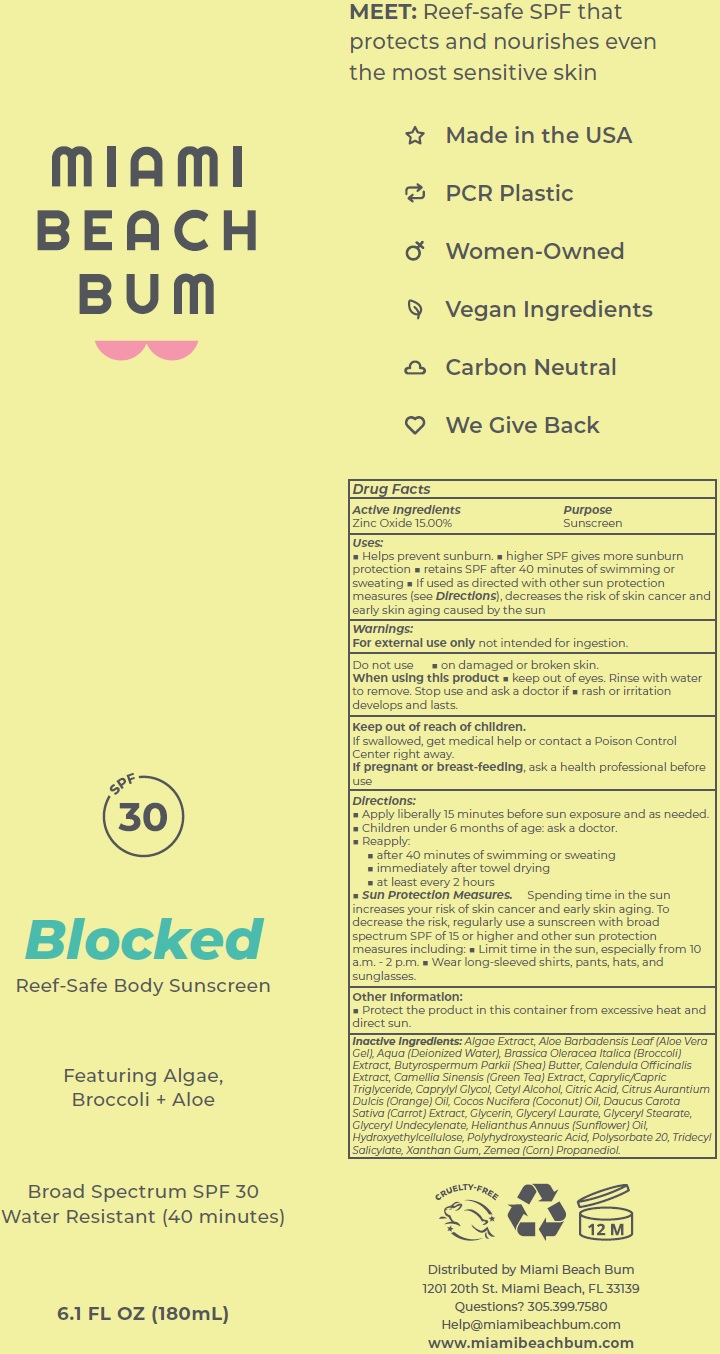 DRUG LABEL: MIAMI BEACH BUM Blocked SPF-30 Sunscreen
NDC: 82812-337 | Form: CREAM
Manufacturer: MIAMI BEACH BUM
Category: otc | Type: HUMAN OTC DRUG LABEL
Date: 20231111

ACTIVE INGREDIENTS: ZINC OXIDE 150 mg/1 mL
INACTIVE INGREDIENTS: ALOE VERA LEAF; WATER; BROCCOLI; SHEA BUTTER; CALENDULA OFFICINALIS FLOWER; GREEN TEA LEAF; MEDIUM-CHAIN TRIGLYCERIDES; CAPRYLYL GLYCOL; CETYL ALCOHOL; CITRIC ACID MONOHYDRATE; ORANGE OIL, COLD PRESSED; COCONUT OIL; CARROT; GLYCERIN; GLYCERYL LAURATE; GLYCERYL MONOSTEARATE; HELIANTHUS ANNUUS FLOWERING TOP; HYDROXYETHYL CELLULOSE, UNSPECIFIED; POLYSORBATE 20; TRIDECYL SALICYLATE; XANTHAN GUM; CORN; PROPANEDIOL

MIAMI BEACH BUM Blocked SPF-30 Sunscreen

Active Ingredients

Zinc Oxide 15.00%

Purpose

Sunscreen

Uses:

- Helps prevent sunburn.
- higher SPF gives more sunburn protection
- retains SPF after 40 minutes of swimming or sweating
- If used as directed with other sun protection measures (see Directions), decreases the risk of skin cancer and early skin aging caused by the sun

Warnings:

not intended for ingestion. For external use only

Do not use

- on damaged or broken skin.

When using this product

- keep out of eyes. Rinse with water to remove. Stop use and ask a doctor if
- rash or irritation develops and lasts.

Keep out of reach of children.

If swallowed, get medical help or contact a Poison Control Center right away.

If pregnant or breast-feeding,

ask a health professional before use

Directions:

- Apply liberally 15 minutes before sun exposure and as needed.
- Children under 6 months of age: ask a doctor.
- Reapply:
- after 40 minutes of swimming or sweating
- immediately after towel drying
- at least every 2 hours
- Spending time in the sun increases your risk of skin cancer and early skin aging. To decrease the risk, regularly use a sunscreen with broad spectrum SPF of 15 or higher and other sun protection measures including: Sun Protection Measures.
- Limit time in the sun, especially from 10 a.m. - 2 p.m.
- Wear long-sleeved shirts, pants, hats, and sunglasses.

Other Information:

- Protect the product in this container from excessive heat and direct sun.

Inactive Ingredients:

Algae Extract, Aloe Barbadensis Leaf (Aloe Vera Gel), Aqua (Deionized Water), Brassica Oleracea Italica (Broccoli) Extract, Butyrospermum Parkii (Shea) Butter, Calendula Officinalis Extract, Camellia Sinensis (Green Tea) Extract, Caprylic/Capric Triglyceride, Caprylyl Glycol, Cetyl Alcohol, Citric Acid, Citrus Aurantium Dulcis (Orange) Oil, Cocos Nucifera (Coconut) Oil, Daucus Carota Sativa (Carrot) Extract, Glycerin, Glyceryl Laurate, Glyceryl Stearate, Glyceryl Undecylenate, Helianthus Annuus (Sunflower) Oil, Hydroxyethylcellulose, Polyhydroxystearic Acid, Polysorbate 20, Tridecyl Salicylate, Xanthan Gum, Zemea (Corn) Propanediol.

Questions?

305.399.7580 Help@miamibeachbum.com
www.miamibeachbum.com